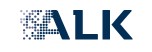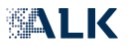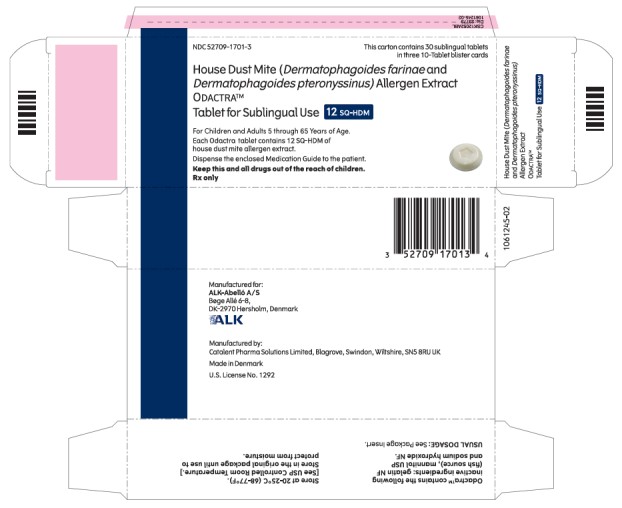 DRUG LABEL: Odactra
NDC: 52709-1701 | Form: TABLET
Manufacturer: ALK-Abello A S
Category: other | Type: STANDARDIZED ALLERGENIC
Date: 20250227

ACTIVE INGREDIENTS: DERMATOPHAGOIDES PTERONYSSINUS 6 [arb'U]/1 1; DERMATOPHAGOIDES FARINAE 6 [arb'U]/1 1
INACTIVE INGREDIENTS: MARINE NON-GELLING GELATIN, HIGH MW; MARINE NON-GELLING GELATIN; MANNITOL; SODIUM HYDROXIDE

HIGHLIGHTS OF PRESCRIBING INFORMATION

These highlights do not include all the information needed to use ODACTRA safely and effectively. See full prescribing information for ODACTRA.
ODACTRA™ House Dust Mite (Dermatophagoides farinae and Dermatophagoides pteronyssinus) Allergen Extract
Tablet for Sublingual Use
Initial U.S. Approval: 2017

RECENT MAJOR CHANGES

Indications and Usage (1) 02/2025

WARNING: SEVERE ALLERGIC REACTIONS

See full prescribing information for complete boxed warning.

•ODACTRA can cause life-threatening allergic reactions such as anaphylaxis and severe laryngopharyngeal restriction. (5.1)

• Do not administer ODACTRA to patients with severe, unstable or uncontrolled asthma. (4)

• Observe patients in the office for at least 30 minutes following the initial dose. (5.1)

•Prescribe epinephrine, instruct and train patients or parents/guardians on its appropriate use, and instruct patients or parents/guardians to seek immediate medical care upon its use. (5.1)

•ODACTRA may not be suitable for patients with certain underlying medical conditions that may reduce their ability to survive a serious allergic reaction. (5.1)

•ODACTRA may not be suitable for patients who may be unresponsive to epinephrine or inhaled bronchodilators, such as those taking beta-blockers. (5.1)

1 INDICATIONS AND USAGE

ODACTRA is an allergen extract indicated as immunotherapy for the treatment of house dust mite (HDM)-induced allergic rhinitis, with or without conjunctivitis, confirmed by positive in vitro testing for IgE antibodies to Dermatophagoides farinae or Dermatophagoides pteronyssinus house dust mites or by positive skin testing to licensed house dust mite allergen extracts. ODACTRA is approved for use in individuals 5 through 65 years of age. (1)

2 DOSAGE AND ADMINISTRATION

For sublingual use only. (2)

- One tablet daily. (2.1)
- Place the tablet immediately under the tongue where it will dissolve within 10 seconds. Allow it to remain there until completely dissolved. Do not swallow for at least 1 minute. (2.2)
- Administer the first dose of ODACTRA under the supervision of a healthcare professional with experience in the diagnosis and treatment of allergic diseases. Observe patients in the office for at least 30 minutes following the initial dose. (2.2)

3 DOSAGE FORMS AND STRENGTHS

- Tablet, 12 SQ-HDM. (3)

4 CONTRAINDICATIONS

- Severe, unstable or uncontrolled asthma. (4)
- History of any severe systemic allergic reaction or any severe local reaction to sublingual allergen immunotherapy. (4)
- A history of eosinophilic esophagitis. (4)
- Hypersensitivity to any of the inactive ingredients contained in this product. (4)

5 WARNINGS AND PRECAUTIONS

- Inform patients or parents/guardians of the signs and symptoms of serious allergic reactions and instruct them to seek immediate medical care and discontinue therapy should any of these occur. (5.1)
- In case of oral inflammation or wounds, stop treatment with ODACTRA to allow complete healing of the oral cavity. (5.6)

6 ADVERSE REACTIONS

- The most common solicited adverse reactions reported in ≥10% of adult participants (18 through 65 years of age) treated with ODACTRA were: throat irritation/tickle, itching in the mouth, itching in the ear, swelling of the uvula/back of the mouth, swelling of the lips, swelling of the tongue, tongue pain, nausea, throat swelling, stomach pain, tongue ulcer/sore on the tongue, mouth ulcer/sore in the mouth, and food tastes different. (6.1)
- The most common solicited adverse reactions reported in ≥10% of adolescent participants (12 through 17 years of age) treated with ODACTRA were: throat irritation/tickle, itching in the mouth, itching in the ear, tongue pain, stomach pain, swelling of the uvula/back of the mouth, swelling of the lips, swelling of the tongue, throat swelling, nausea, tongue ulcer/sore on the tongue, and mouth ulcer/sore in the mouth, and diarrhea. (6.1)
- The most common solicited adverse reactions reported in ≥10% of pediatric participants (5 through 11 years of age) treated with ODACTRA were: itching in the mouth, throat irritation/tickle, itching in the ear, stomach pain, swelling of the lips, tongue pain, food tastes different, nausea (feel like throwing up), swelling in the back of the mouth, swelling of the tongue, and mouth ulcer. (6.1)

To report SUSPECTED ADVERSE REACTIONS, contact ALK-Abelló Inc., a subsidiary of ALK-Abelló A/S, at 1-855-216-6497 or FDA at 1-800-FDA-1088 or www.fda.gov/medwatch.

FULL PRESCRIBING INFORMATION

WARNING: SEVERE ALLERGIC REACTIONS

- ODACTRA can cause life-threatening allergic reactions such as anaphylaxis and severe laryngopharyngeal restriction. (5.1)
- Do not administer ODACTRA to patients with severe, unstable or uncontrolled asthma. (4)
- Observe patients in the office for at least 30 minutes following the initial dose. (5.1)
- Prescribe epinephrine, instruct and train patients or parents/guardians on its appropriate use, and instruct patients or parents/guardians to seek immediate medical care upon its use. (5.1)
- ODACTRA may not be suitable for patients with certain underlying medical conditions that may reduce their ability to survive a serious allergic reaction. (5.1)
- ODACTRA may not be suitable for patients who may be unresponsive to epinephrine or inhaled bronchodilators, such as those taking beta-blockers. (5.1)

1 INDICATIONS AND USAGE

ODACTRA™ is an allergen extract indicated as immunotherapy for the treatment of house dust mite (HDM)-induced allergic rhinitis, with or without conjunctivitis, confirmed by positive in vitro testing for IgE antibodies to Dermatophagoides farinae or Dermatophagoides pteronyssinus house dust mites, or by positive skin testing to licensed house dust mite allergen extracts. ODACTRA is approved for use in individuals 5 through 65 years of age.

ODACTRA is not indicated for the immediate relief of allergic symptoms.

2 DOSAGE AND ADMINISTRATION

For sublingual use only.

2.1 Dose

One ODACTRA tablet daily.

2.2 Administration

Administer the first dose of ODACTRA in a healthcare setting under the supervision of a healthcare professional with experience in the diagnosis and treatment of allergic diseases. After receiving the first dose of ODACTRA, observe the patient for at least 30 minutes to monitor for signs or symptoms of a severe systemic or a severe local allergic reaction. If the patient tolerates the first dose, the patient may take subsequent doses at home. The patient should administer ODACTRA as follows:

- Take the tablet from the blister unit after carefully removing the foil with dry hands.
- Place the tablet immediately under the tongue where it will dissolve within 10 seconds. Do not swallow for at least 1 minute.
- Wash hands after handling the tablet.
- Do not take the tablet with food or beverage. Food or beverage should not be taken for 5 minutes after taking the tablet.

Data regarding the safety of restarting treatment after missing a dose of ODACTRA are limited. In the clinical studies, treatment interruptions for up to seven days were allowed. Prescribe epinephrine to patients prescribed ODACTRA and instruct patients (or their parents/guardians) in the proper use of epinephrine [see Warnings and Precautions (5.1)].

3 DOSAGE FORMS AND STRENGTHS

ODACTRA is available as 12 SQ-HDM* tablets that are white to off-white, circular with a debossed pentagon detail on one side.

*SQ-HDM is the dose unit for ODACTRA. SQ is a method of standardization of biological potency, major allergen content and complexity of the allergen extract. HDM is an abbreviation for house dust mite.

4 CONTRAINDICATIONS

ODACTRA is contraindicated in patients with:

- Severe, unstable or uncontrolled asthma
- A history of any severe systemic allergic reaction
- A history of any severe local reaction after taking any sublingual allergen immunotherapy
- A history of eosinophilic esophagitis
- Hypersensitivity to any of the inactive ingredients contained in this product [see Description (11)]

5 WARNINGS AND PRECAUTIONS

5.1 Severe Allergic Reactions

ODACTRA can cause systemic allergic reactions including anaphylaxis which may be life-threatening. In addition, ODACTRA can cause severe local reactions, including laryngopharyngeal swelling, which can compromise breathing and be life-threatening.

Allergic reactions may require treatment with epinephrine. Prescribe epinephrine to patients receiving ODACTRA. Instruct patients or their parents/guardians to recognize the signs and symptoms of a severe allergic reaction and in the proper use of emergency epinephrine. Instruct patients or their parents/guardians to seek immediate medical care and to stop treatment with ODACTRA upon use of epinephrine [see Patient Counseling Information (17)]. See Prescribing Information for epinephrine for complete information.

ODACTRA may not be suitable for patients with certain medical conditions that may reduce the ability to survive a serious allergic reaction or that may increase the risk of adverse reactions after epinephrine administration. Examples of these medical conditions include but are not limited to: markedly compromised lung function (either chronic or acute); severe mast cell disorder; or cardiovascular disease including unstable angina, recent myocardial infarction, significant arrhythmia, and uncontrolled hypertension. In addition, ODACTRA may not be suitable for patients who are taking medications that can potentiate or inhibit the effects of epinephrine (see Prescribing Information for epinephrine for information on drug interactions).

Administer the initial dose of ODACTRA in a healthcare setting under the supervision of a healthcare professional with experience in the diagnosis and treatment of allergic diseases and prepared to manage a life-threatening systemic or local allergic reaction. Observe patients in the office for at least 30 minutes following the initial dose of ODACTRA.

5.2 Upper Airway Compromise

ODACTRA can cause local reactions in the mouth or throat that could compromise the upper airway [see Adverse Reactions (6.1)]. Consider discontinuation of ODACTRA in patients who experience persistent and escalating adverse reactions in the mouth or throat.

5.3 Eosinophilic Esophagitis

Eosinophilic esophagitis has been reported in association with sublingual tablet immunotherapy [see Contraindications (4)]. Discontinue ODACTRA and consider a diagnosis of eosinophilic esophagitis in patients who experience severe or persistent gastroesophageal symptoms including dysphagia or chest pain.

5.4 Asthma

Withhold immunotherapy with ODACTRA if the patient is experiencing an acute asthma exacerbation. Re-evaluate patients who have recurrent asthma exacerbations and consider discontinuation of ODACTRA.

5.5 Concomitant Allergen Immunotherapy

ODACTRA has not been studied in participants who are receiving concomitant allergen immunotherapy. Concomitant dosing with other allergen immunotherapy may increase the likelihood of local or systemic adverse reactions to either subcutaneous or sublingual allergen immunotherapy.

5.6 Oral Conditions

Stop treatment with ODACTRA to allow complete healing of the oral cavity in patients with oral inflammation (e.g., oral lichen planus, mouth ulcers, or thrush) or oral wounds, such as those following oral surgery, tooth loss or dental extraction.

6 ADVERSE REACTIONS

The most common solicited adverse reactions reported in ≥10% of adult participants (18 through 65 years of age) treated with ODACTRA were: throat irritation/tickle, itching in the mouth, itching in the ear, swelling of the uvula/back of the mouth, swelling of the lips, swelling of the tongue, tongue pain, nausea, throat swelling, stomach pain, tongue ulcer/sore on the tongue, mouth ulcer/sore in the mouth, and food tastes different.

The most common solicited adverse reactions reported in ≥10% of adolescent participants (12 through 17 years of age) treated with ODACTRA were: throat irritation/tickle, itching in the mouth, itching in the ear, tongue pain, stomach pain, swelling of the uvula/back of the mouth, swelling of the lips, swelling of the tongue, throat swelling, nausea, tongue ulcer/sore on the tongue, and mouth ulcer/sore in the mouth, and diarrhea.

The most common solicited adverse reactions reported in ≥10% of pediatric participants (5 through 11 years of age) treated with ODACTRA were itching in the mouth, throat irritation/tickle, itching in the ear, stomach pain, swelling of the lips, tongue pain, food tastes different, nausea (feel like throwing up), swelling in the back of the mouth, swelling of the tongue, and mouth ulcer.

6.1 Clinical Trials Experience

Because clinical trials are conducted under widely varying conditions, adverse reaction rates observed in the clinical trials of a drug cannot be directly compared to rates in the clinical trials of another drug and may not reflect the rates observed in clinical practice.

Adults (18 through 65 years of age)

In four double-blind, placebo-controlled, randomized clinical studies, a total of 1279 participants with house dust mite-induced allergic rhinitis, with or without conjunctivitis, 18 through 65 years of age was treated with at least one dose of ODACTRA 12 SQ-HDM. Of participants treated with ODACTRA in the four studies, 50% had mild to moderate asthma and 71% were polysensitized to other allergens in addition to HDM, including trees, grasses, weeds, molds, and animal danders. The study population was 88% White, 6% African American, 4% Asian and 55% female.

Study 1 (NCT01700192) was a randomized, double-blind, placebo-controlled study conducted in the US and Canada evaluating ODACTRA in 1482 participants 12 years of age and older with house dust mite-induced allergic rhinitis with or without conjunctivitis. Of the 1482 participants, 640 participants 18 through 65 years of age received at least one dose of ODACTRA, with a median treatment duration of 267 days (range 1 to 368 days). 631 participants received placebo. Placebo tablets contained the same inactive ingredients as ODACTRA without allergen extract and were packaged identically so that treatment blind/masking was maintained. Participants were monitored for unsolicited adverse events and serious adverse events (SAEs) for the duration of therapy (up to 52 weeks). Participants were monitored for solicited adverse reactions for the first 28 days following treatment initiation.

Study participants were provided side effect report cards in which they recorded the occurrence of specific solicited adverse reactions daily for the first 28 days following treatment initiation with ODACTRA or placebo. In Study 1, the most common solicited adverse reactions reported in ≥10% of participants treated with ODACTRA were: throat irritation/tickle (67.0% vs. 20.8% placebo), itching in the mouth (61.3% vs. 14.1%), itching in the ear (51.7% vs. 11.7%), swelling of the uvula/back of the mouth (19.8% vs. 2.4%), swelling of the lips (18.0% vs. 2.7%), swelling of the tongue (15.8% vs. 2.1%), nausea (14.2% vs. 7.1%), tongue pain (14.2% vs. 3.0%), throat swelling (13.6% vs. 2.4%), tongue ulcer/sore on the tongue (11.6% vs. 2.1%), stomach pain (11.3% vs. 5.2%), mouth ulcer/sore in the mouth (10.3% vs. 2.9%), and taste alteration/food tastes different (10.0% vs. 3.6%). Table 1 summarizes all solicited adverse reactions reported within the first 28 days of treatment initiation in participants 18 through 65 years of age using the patient-friendly term.

Table 1: Solicited* Adverse Reactions Occurring Within 28 Days After Initiation of Treatment with ODACTRA or Placebo (Study 1, Safety Analysis Set) in Participants 18 through 65 Years of Age
Adverse Reaction | Any Intensity |  | Severe†
 | ODACTRA (N=640) | Placebo (N=631) | ODACTRA (N=640) | Placebo (N=631)
Ear and labyrinth disorders
Itching in the ear | 51.7% | 11.7% | 0.3% | -
Gastrointestinal disorders
Itching in the mouth | 61.3% | 14.1% | 0.2% | -
Swelling of the uvula/back of the mouth‡ | 19.8% | 2.4% | - | -
Swelling of the lips | 18.0% | 2.7% | - | -
Swelling of the tongue | 15.8% | 2.1% | - | -
Nausea | 14.2% | 7.1% | - | -
Tongue pain | 14.2% | 3.0% | - | -
Tongue ulcer/sore on the tongue | 11.6% | 2.1% | - | -
Stomach pain | 11.3% | 5.2% | 0.2% | -
Mouth ulcer/sore in the mouth | 10.3% | 2.9% | - | -
Diarrhea | 6.9% | 3.6% | - | -
Vomiting | 2.5% | 1.4% | - | -
Nervous system disorders
Taste alteration/food tastes different | 10.0% | 3.6% | - | -
Respiratory, thoracic and mediastinal disorders
Throat irritation/tickle | 67.0% | 20.8% | 0.3% | -
Throat swelling | 13.6% | 2.4% | 0.2% | -

In Table 1, the dashes represent no participants.

*Solicited adverse reactions (modified from World Allergy Organization [WAO] list of local side effects of sublingual immunotherapy [SLIT]) were those reported by participants within the first 28 days after treatment initiation.

†Severe adverse reactions were those assessed by the investigator as severe in intensity, which is defined as incapacitating with inability to work or do usual activity.

‡The percentage of participants reported for the patient-friendly term of "swelling of the uvula/back of the mouth" includes participants with an enlarged uvula, palatal swelling/edema, and/or mouth swelling/edema (which can be anywhere in the mouth, not specifically back of the mouth).

In Study 1, the timing of the adverse reaction relative to exposure to ODACTRA was evaluated for 7 solicited adverse reactions (itching in the ear, itching in the mouth, swelling of the uvula/back of the mouth, swelling of the lips, swelling of the tongue, throat irritation/tickle, and throat swelling). The median time to onset of these adverse reactions following initiation of treatment with ODACTRA varied from 1 to 7 days. The median duration of these adverse reactions that occurred on the first day of treatment initiation varied from 30 to 60 minutes. These adverse reactions recurred for a median of 2 to 12 days.

In Study 1, the following unsolicited adverse events were reported in numerically more participants treated with ODACTRA than with placebo and occurred in ≥1% of participants 18 through 65 years of age within 28 days after initiation of treatment with ODACTRA: paresthesia oral (9.2% vs. 3.2%), tongue pruritus (4.7% vs. 1.1%), oral pain (2.7% vs. 0.6%), stomatitis (2.5% vs. 1.1%), dyspepsia (2.2% vs. 0.0%), pharyngeal erythema (2.0% vs. 0.3%), eye pruritus (1.7% vs. 1.4%), oral mucosal erythema (1.7% vs. 0.2%), upper respiratory tract infection (1.6% vs. 1.1%), sneezing (1.6% vs. 0.3%), lip pruritus (1.4% vs. 0.3%), dysphagia (1.4% vs. 0.0%), fatigue (1.3% vs. 1.0%), hypoesthesia oral (1.3% vs. 1.0%), oropharyngeal pain (1.3% vs. 0.6%), chest discomfort (1.3% vs. 0.3%), dry throat (1.3% vs. 0.3%), pruritus (1.1% vs. 1.0%), and urticaria (1.1% vs. 0.3%).

Studies 2 (NCT01454544) and 3 (NCT01644617) were randomized, double-blind, placebo-controlled studies of participants 18 years of age and older with house dust mite-induced allergic rhinitis with or without conjunctivitis, and with or without asthma. Study 4 (NCT01433523) was a randomized, double-blind placebo-controlled study that included participants 18 years of age and older with house dust mite-induced asthma and allergic rhinitis, with or without conjunctivitis.

Across the four clinical studies, 1279 participants received at least one dose of ODACTRA, of whom 1104 (86%) completed at least 4 months of therapy.

The percentages of participants in these studies who discontinued treatment because of an adverse reaction while exposed to ODACTRA or placebo were 8.1% and 3.0%, respectively. The most common adverse reactions (≥1.0%) that led to study discontinuation in participants who received ODACTRA were throat irritation (1.5%), oral pruritus (1.3%), ear pruritus (1.1%), and mouth swelling (1.0%).

Serious adverse events were reported, 16/1279 (1.3%) among ODACTRA recipients and 23/1277 (1.8%) among placebo recipients. No deaths were reported.

Epinephrine use was reported in 5/1279 (0.4%) participants who received ODACTRA compared to 3/1277 (0.2%) of participants who received placebo. Of these participants, 1 ODACTRA recipient reported a systemic allergic reaction and used epinephrine on the day of treatment initiation compared to 2 placebo recipients who reported anaphylaxis and used epinephrine 6 and 25 days after treatment initiation, respectively.

Of 1279 participants who received ODACTRA, 34 (2.7%) reported dyspepsia compared to 0/1277 (0%) of participants who received placebo. Twenty participants who received ODACTRA (1.6%) reported symptoms of gastroesophageal reflux disease (GERD) compared to 3/1277 (0.2%) of participants who received placebo.

Adolescents (12 through 17 years of age)

In two clinical studies, a total of 347 adolescent participants were treated with at least one dose of ODACTRA. Study 1 (NCT01700192) was a double-blind, placebo-controlled, randomized clinical study. Study 5 (NCT04541004) was a single arm, open-label safety study. Because the study design and safety data presentation differ in the studies, adverse reaction rates cannot be directly compared. Overall, the safety profile in adolescents was consistent with the safety profile in adults.

Study 1 was a randomized, double-blind, placebo-controlled study conducted in the US and Canada evaluating ODACTRA in 1482 participants 12 years of age and older with house dust mite-induced allergic rhinitis with or without conjunctivitis. Of the 1482 participants, 94 participants 12 through 17 years of age received at least one dose of ODACTRA, with a median treatment duration of 279 days (range 1 to 353 days). 95 participants received placebo. Of the adolescent participants treated with ODACTRA, 53% were male, 39% had asthma, and 72% were polysensitized to other allergens in addition to HDM. The adolescent participant population was 69% White, 13% Black or African American, 10% multiple race, 5% Asian, and 3% American Indian or Alaska Native. Participant demographics in placebo-treated participants were similar to the active treatment group.

In Study 1, study participants were provided side effect report cards in which they recorded the occurrence of specific solicited adverse reactions daily for the first 28 days following treatment initiation with ODACTRA or placebo. The solicited adverse reactions reported in adolescent participants 12 through 17 years of age are summarized in Table 2.

Table 2: Solicited* Adverse Reactions Occurring Within 28 Days After Initiation of Treatment with ODACTRA or Placebo (Study 1, Safety Analysis Set) in Participants 12 through 17 Years of Age
Adverse Reaction (Any Intensity‡) | ODACTRA (N=94) | Placebo (N=95)
Ear and labyrinth disorders
Itching in the ear | 50.0% | 11.6%
Gastrointestinal disorders
Itching in the mouth‡ | 73.4% | 14.7%
Tongue pain | 24.5% | 4.2%
Stomach pain | 23.4% | 15.8%
Swelling of the uvula/back of the mouth† | 20.2% | 3.2%
Swelling of the lips | 20.2% | 1.1%
Swelling of the tongue | 19.1% | 3.2%
Nausea‡ | 17.0% | 9.5%
Tongue ulcer/sore on the tongue | 12.8% | 4.2%
Mouth ulcer/sore in the mouth | 10.6% | 3.2%
Diarrhea | 7.7% | 2.1%
Vomiting‡ | 4.3% | -
Nervous system disorders
Taste alteration/food tastes different | 4.3% | 4.2%
Respiratory, thoracic and mediastinal disorders
Throat irritation/tickle‡ | 73.4% | 35.8%
Throat swelling | 18.1% | 8.4%

In Table 2, the dashes represent no participants.

*Solicited adverse reactions (modified from World Allergy Organization [WAO] list of local side effects of sublingual immunotherapy [SLIT]) were those reported by participants within the first 28 days after treatment initiation.

†The percentage of participants reported for the patient-friendly term of "swelling of the uvula/back of the mouth" includes participants with an enlarged uvula, palatal swelling, and/or mouth swelling/edema (which can be anywhere in the mouth, not specifically back of the mouth).

‡Of those participants reporting any intensity of: itching in the mouth, nausea, throat irritation/tickle, or vomiting in the ODACTRA group, 1 participant (1.1%) reported severe intensity of the reaction. Adverse reactions were categorized as severe according to the definition ‘incapacitating with inability to work or do usual activity’, as assessed by the investigator.

In Study 1, participants were monitored for unsolicited adverse events and serious adverse events (SAEs) for the duration of treatment (up to 52 weeks). Unsolicited adverse events that were reported in numerically more participants treated with ODACTRA than with placebo and occurred in ≥1% of participants 12 through 17 years of age within 28 days after initiation of treatment with ODACTRA are summarized in Table 3.

In Study 1, 94 adolescent participants received at least one dose of ODACTRA, of whom 81 (86%) completed at least 4 months of treatment.

The percentage of adolescent participants who discontinued from the study because of an adverse reaction while exposed to ODACTRA or placebo was 10% and 1%, respectively. The most common adverse reaction that led to study discontinuation in adolescent participants who were exposed to ODACTRA were throat irritation (4%), swollen tongue (2%) and nausea (2%).

No adolescent participants treated with ODACTRA in Study 1 reported serious adverse events, treatment-related systemic allergic reactions, or adverse reactions treated with epinephrine.

Table 3: Unsolicited Adverse Reactions Occurring During the Entire Trial After Initiation of Treatment with ODACTRA or Placebo (Study 1, Safety Analysis Set) Reported in ≥1% of Participants 12 through 17 Years of Age
Adverse Reaction | ODACTRA (N=94)† | Placebo (N=95)†
Ear and labyrinth disorders
Ear discomfort | 1.1% | -
Ear pain | 1.1% | -
Eye disorders
Eye pruritus | 1.1% | -
Eye swelling | 1.1% | -
Gastrointestinal disorders
Paraesthesia oral | 5.3% | -
Oral pain | 4.3% | -
Tongue pruritus | 3.2% | -
Stomatitis | 2.1% | 1.1%
Aphthous ulcer | 1.1% | -
Dysphagia | 1.1% | -
Eosinophilic esophagitis | 1.1% | -
Salivary gland enlargement | 1.1% | -
Tongue discomfort | 1.1% | -
General disorders and administration site conditions
Chest discomfort | 2.1% | -
Chest pain | 1.1% | -
Non-cardiac chest pain | 1.1% | -
Infections and infestations
Acute sinusitis | 1.1% | -
Musculoskeletal and connective tissue disorders
Arthralgia | 1.1% | -
Neck pain | 1.1% | -
Respiratory, thoracic and mediastinal disorders
Oropharyngeal pain | 1.1% | -
Rhinorrhea | 1.1% | -
Throat tightness | 1.1% | -
Tonsillar hypertrophy | 1.1% | -
Skin and subcutaneous tissue disorders
Pruritus | 2.1% | 1.1%
Vascular disorders
Flushing | 1.1% | -

In Table 3, the dashes represent no participants.

† Due to the population size (ODACTRA; N=94; and placebo; N=95), 1.1% represents one participant.

Study 5 (NCT04541004) was a single-arm, open label study conducted in Europe, and exposed 253 participants 12 through 17 years of age with house dust mite-induced allergic rhinitis with or without conjunctivitis and with or without asthma to at least one dose of ODACTRA. The median treatment duration was 28 days (range 11 to 32 days). Of the participants, 60% were male, 43% had asthma, and 56% were polysensitized to other allergens in addition to HDM. The participant population was 99.6% White and 0.4% Native Hawaiian or Other Pacific Islander.

Study participants were provided side effect report cards in which they recorded the occurrence of specific solicited adverse reactions daily for the first 28 days following treatment initiation with ODACTRA or placebo. Participants were monitored for unsolicited adverse events and serious adverse events (SAEs) for the duration of the study.

In Study 5, the proportions of participants reporting solicited adverse reactions during the first 28 days following initiation of treatment with ODACTRA were comparable to those reported during the first 28 days following initiation of treatment with ODACTRA in Study 1.

In Study 5, the following unsolicited adverse reactions occurred in ≥1% of participants 12 through 17 years of age during the entire study [median treatment duration 28 days (range 11 to 32 days)] after initiation of treatment with ODACTRA: oral pain (3.2%), oral pruritus (2.8%), throat irritation (1.6%), ear pruritus (1.2%), and mouth ulceration (1.2%).

In Study 5, 253 adolescent participants received at least one dose of ODACTRA, of whom 248 (98%) completed 28 days of treatment. The percentage of participants who discontinued from the study because of an adverse reaction while exposed to ODACTRA was 1%.

No adolescent participants in Study 5 reported serious adverse events, treatment-related systemic allergic reactions, or adverse reactions treated with epinephrine.

Children (5 through 11 years of age)

Study 6 (NCT04145219) was a randomized, double-blind, placebo-controlled study conducted in Europe, US and Canada evaluating ODACTRA in 1458 participants 5 through 11 years of age with house dust mite-induced allergic rhinitis/rhinoconjunctivitis with or without asthma. Of the 1458 participants, 727 participants received at least one dose of ODACTRA, with a median treatment duration of 378 days (range 1 to 486 days) and 731 participants received placebo, with a median treatment duration of 379 days (range 1 to 449 days). Placebo tablets contained the same inactive ingredients as ODACTRA without allergen extract. Of the participants treated with ODACTRA, mean age was 8 years, 67% were male, 99% White, <1% Black or African American, <1% multiple race, <1% Asian, and <1% American Indian or Alaska Native. Participant demographics in the placebo group were similar to the ODACTRA group. In the ODACTRA group, 37% of participants had asthma and 54% were sensitized to other allergens in addition to HDM; the treatment groups were similar with respect to these baseline characteristics.

In Study 6, participants were provided an eDiary in which they recorded the occurrence of specific solicited adverse reactions daily for the first 28 days following treatment initiation with ODACTRA or placebo.The investigator reviewed the symptoms with the participant and determined if they were possibly related to the study treatment. The solicited adverse reactions reported in pediatric participants 5 through 11 years of age are summarized in Table 4.

Table 4: Solicited Adverse Reactions* Occurring Within 28 Days After Initiation of Treatment with ODACTRA or Placebo (Study 6, Safety Analysis Set) in Participants 5 through 11 Years of Age
Adverse Reaction | Any Intensity |  | Severe†
 | ODACTRA (N=727) | Placebo (N=731) | ODACTRA (N=727) | Placebo (N=731)
Ear and labyrinth disorders
Itching in the ear | 32.7% | 17.0% | 0.1% | -
Gastrointestinal disorders
Itching in the mouth | 57.1% | 23.9% | 0.1% | -
Stomach pain | 28.2% | 15.7% | 0.1% | -
Swelling of the lips | 20.5% | 4.9% | 0.3% | -
Tongue pain | 19.4% | 5.2% | 0.1% | -
Nausea (feel like throwing up) | 15.7% | 9.0% | - | -
Swelling in the back of the mouth | 13.5% | 3.3% | - | -
Swelling of the tongue | 13.5% | 2.6% | - | -
Mouth ulcer | 10.0% | 6.4% | - | -
Diarrhea | 8.0% | 5.9% | - | -
Tongue ulcer | 6.3% | 3.4% | - | -
Vomiting | 4.5% | 2.2% | - | -
Nervous system disorders
Food tastes different | 16.0% | 14.5% | - | -
Respiratory, thoracic and mediastinal disorders
Throat irritation/tickle | 55.2% | 31.5% | - | -
Throat swelling | 9.2% | 2.9% | - | -

In Table 4, the dashes represent no participants.

*Solicited adverse reactions (modified from World Allergy Organization [WAO] list of local side effects of sublingual immunotherapy [SLIT]) were those reported by participants within the first 28 days after treatment initiation and determined by the investigator to be possibly related to the study treatment.

†Severe adverse reactions were those assessed by the investigator as severe in intensity, which is defined as incapacitating with inability to work or do usual activity.

In Study 6, participants 5 through 11 years of age were monitored for unsolicited adverse events and SAEs for the entire duration of treatment (approximately 12 months). Unsolicited adverse reactions that were commonly reported (≥1%) and for which the rate for ODACTRA exceeded the rate for placebo are presented in Table 5.

Table 5: Unsolicited Adverse Reactions Occurring During the Entire Trial After Initiation of Treatment with ODACTRA or Placebo (Study 6, Safety Analysis Set) Reported in ≥1% of Participants 5 through 11 Years of Age
Adverse Reaction | ODACTRA (N=727) | Placebo (N=731)
Ear and labyrinth disorders
Ear pruritus | 1.5% | 0.4%
Gastrointestinal disorders
Oral pruritus | 5.4% | 1.1%
Abdominal pain upper | 1.5% | 0.7%
Nausea | 1.1% | 0.3%
Respiratory, thoracic and mediastinal disorders
Throat irritation | 3.4% | 1.4%

In Table 5, the events are presented by SOC and PT.

In Study 6, 727 participants received at least one dose of ODACTRA, of whom 702 (97%) completed at least 3 months of treatment.

The percentage of participants who discontinued the study treatment because of an adverse reaction while exposed to ODACTRA or placebo was 1.8% and 1.0%, respectively. The most common adverse reactions that led to study discontinuation in participants who were exposed to ODACTRA were nausea (0.6%), lip swelling (0.4%) and throat irritation (0.4%).

No participants treated with ODACTRA in Study 6 reported treatment-related serious adverse events, treatment-related anaphylaxis, or adverse reactions treated with epinephrine.

Across twelve clinical studies in which individuals 5 through 85 years of age received ODACTRA or tablets containing different quantities of the same house dust mite allergen extracts and inactive ingredients as ODACTRA, eosinophilic esophagitis was reported in 3/4614 (0.07%) participants; no cases of eosinophilic esophagitis were reported among 2949 (0%) participants who received placebo. The three cases of eosinophilic esophagitis were assessed as related to study treatment. One case, which was reported as an SAE, occurred in a 10 year old participant on Day 31 of treatment. The other cases occurred in a 13 year old participant and a 34 year old participant on Day 204 and Day 99 of treatment, respectively.

6.2 Postmarketing Experience

The following adverse reactions have been identified during post-approval use of ODACTRA. Because these reactions are reported voluntarily from a population of uncertain size, it is not always possible to reliably estimate their frequency or establish a causal relationship to drug exposure.

- Gastrointestinal disorder: esophageal irritation
- General Disorders and Administration Site Conditions: sensation of foreign body
- Immune System Disorders: serious systemic allergic reactions, including anaphylaxis
- Respiratory, Thoracic and Mediastinal Disorders: asthma exacerbations, cough, dysphonia
- Skin and Subcutaneous Tissue Disorders: angioedema, erythema.

8 USE IN SPECIFIC POPULATIONS

8.1 Pregnancy

Risk Summary

All pregnancies have a risk of birth defect, loss, or other adverse outcomes. In the U.S. general population, the estimated background risk of major birth defects and miscarriage in clinically recognized pregnancies is 2% to 4% and 15% to 20%, respectively. Available data on ODACTRA administered to pregnant women are insufficient to inform associated risks in pregnancy.

In an embryo/fetal developmental toxicity study performed in mice, administration of ODACTRA during gestation did not reveal adverse developmental outcomes in fetuses [see Data (8.1)].

Data

Animal Data

In a developmental toxicity study, the effect of ODACTRA on embryo/fetal development was evaluated in mice. Animals were administered ODACTRA subcutaneously daily from day 6 to day 17 of the gestation period at doses up to 5 times the human sublingual dose. There were no ODACTRA-related post-implantation losses, fetal malformations or variations.

8.2 Lactation

Risk Summary

It is not known whether ODACTRA is excreted in human milk. Data are not available to assess the effects of ODACTRA on the breastfed child or on milk production and excretion in the nursing woman. The developmental and health benefits of breastfeeding should be considered along with the mother’s clinical need for ODACTRA and any potential adverse effects on the breastfed child from ODACTRA or from the underlying maternal condition.

8.4 Pediatric Use

The safety and effectiveness of ODACTRA have been established in individuals 5 through 17 years of age with HDM-induced allergic rhinitis, with or without conjunctivitis. [see Adverse Reactions (6.1) and Clinical Studies (14)].

The safety and effectiveness have not been established in individuals below 5 years of age.

8.5 Geriatric Use

Safety and effectiveness have not been established in individuals older than 65 years of age.

10 OVERDOSAGE

Symptoms of overdose may include hypersensitivity reactions such as systemic allergic reactions or severe local allergic reactions [see Warnings and Precautions (5.1)]. In case of severe adverse reactions such as angioedema, difficulty in swallowing, difficulty in breathing, changes in voice, or feeling of fullness in the throat, immediate medical evaluation is needed. These reactions should be treated as medically indicated, including the use of epinephrine as appropriate [see Warnings and Precautions (5.1)].

11 DESCRIPTION

ODACTRA tablets contain house dust mite allergen extract from Dermatophagoides farinae and Dermatophagoides pteronyssinus. ODACTRA is a sublingual tablet that dissolves within 10 seconds.

ODACTRA is available as a tablet of 12 SQ-HDM [6 SQ-HDM D. farinae and 6 SQ-HDM D. pteronyssinus]. Each tablet contains a 1:1:1:1 potency ratio of D. farinae group 1 allergen, D. farinae group 2 allergen, D. pteronyssinus group 1 allergen, and D. pteronyssinus group 2 allergen.

Inactive ingredients: gelatin NF (fish source), mannitol USP, and sodium hydroxide NF.

12 CLINICAL PHARMACOLOGY

12.1 Mechanism of Action

The precise mechanisms of action of allergen immunotherapy have not been fully established.

13 NONCLINICAL TOXICOLOGY

13.1 Carcinogenesis, Mutagenesis, Impairment of Fertility

ODACTRA has not been evaluated for carcinogenic potential or impairment of fertility in animals. Two in vitro chromosome aberration assays, an in vitro bacterial mutagenesis assay and a combined in vivo Comet and micronucleus assay for mutagenicity in rats were performed using HDM (D. farinae and D. pteronyssinus) allergen extracts. One in vitro chromosome aberration assay was positive. Based on the aggregated results, the weight of evidence indicates that this finding is unlikely to be of clinical relevance.

14 CLINICAL STUDIES

The efficacy of ODACTRA for the treatment of HDM-induced allergic rhinitis was investigated in three double-blind, placebo-controlled, randomized clinical field efficacy studies (Studies 1, 2, and 6) and one environmental exposure chamber (EEC) study (Study 3).

Adolescents and Adults

Study 1 (North American Field Efficacy Study)

Study 1 was a double-blind, placebo-controlled, randomized field efficacy study conducted in the United States and Canada for a duration of up to 12 months, that compared the efficacy of ODACTRA (N=741) compared to placebo (N=741) in the treatment of HDM-induced allergic rhinitis. Participants 12 through 85 years of age were enrolled if they had a history of symptomatic allergic rhinitis and were sensitized to D. farinae and/or D. pteronyssinus as determined by house dust mite specific IgE. Participants were required to be symptomatic and were not taking symptom-relieving allergy medications at enrollment.

Participants with mild to moderate asthma, defined as asthma of a severity that required, at most, a daily medium dose of an inhaled corticosteroid, were enrolled in the study.

In this study, 31% of participants had asthma, 48% had conjunctivitis, and 76% were polysensitized to other allergens in addition to HDM, including trees, grasses, weed, animal danders and molds. The participant population was 76% White, 11% African American, 7% Asian, and 59% female. The mean age of participants was 35 years.

The efficacy of ODACTRA in the treatment of HDM-induced allergic rhinitis was assessed through self-reporting of symptoms and medication use. Based on these self-assessments, the Total Combined Rhinitis Score (TCRS), daily symptom scores (DSS) and daily medication scores (DMS) for rhinoconjunctivitis were calculated. Daily symptoms included four nasal symptoms (runny nose, stuffy nose, sneezing, and itchy nose) and two ocular symptoms (gritty/itchy eyes and watery eyes). Each of these rhinoconjunctivitis symptoms was individually graded by participants daily on a scale of 0 (none) to 3 (severe) and then summed. Participants in active and placebo arms of this study were allowed to take symptom-relieving allergy medications (including oral and ocular antihistamines and nasal corticosteroids) during the study as needed. The DMS measured the use of these standard symptom-relieving allergy medications. Predefined daily maximum scores were assigned to each class of rhinitis and conjunctivitis medication as 0=none, 6=oral antihistamine, 6=ocular antihistamine, and 8=nasal corticosteroid.

The primary endpoint was the difference between the treatment and placebo groups in the average TCRS during approximately the last 8 weeks of treatment. The TCRS represents the sum of the daily rhinitis DSS and the rhinitis DMS. Other secondary endpoints in this study included the average rhinitis DSS, the average rhinitis DMS, and the Total Combined Score (TCS). The TCS represents the sum of the rhinoconjunctivitis DSS and the rhinoconjunctivitis DMS, which was then averaged during approximately the last 8 weeks of treatment.

Participants in this study were required to stop taking symptom-relieving allergy medication during the baseline period. The mean rhinitis DSS at baseline was 7.94 out of 12 total points in both the treatment arm and in the placebo arm. The results of this study are shown in Table 6. Consistent results across age groups were observed, supporting a similar treatment effect in adolescent and adult subgroups.

Table 6: Total Combined Rhinitis Score (TCRS), Rhinitis Daily Symptom Score (DSS), Rhinitis Daily Medication Score (DMS), and Total Combined Score (TCS) During the Last 8 Weeks of Treatment with ODACTRA in Participants 12 Years of Age and Older (Study 1, Field Efficacy Study)
Endpoint* | ODACTRA (n=566)† Score‡ | Placebo (n=620)† Score‡ | Treatment Difference (ODACTRA- Placebo) | Difference Relative to Placebo§ Estimate (95% CI)
Primary Endpoint
TCRS¶ | 4.10 | 4.95 | -0.80 | -17.2% (-25.0%, -9.7%)
Secondary Endpoints
Rhinitis DSS | 3.55 | 4.20 | -0.60 | -15.5% (-24.4%, -7.3%)
Rhinitis DMS | 0.65 | 0.79 | -0.15 | -18.4% (-41.0%, 4.3%)
TCS | 5.50 | 6.60 | -1.10 | -16.7% (-24.6%, -4.0%)

TCRS=Total Combined Rhinitis Score (Rhinitis DSS + Rhinitis DMS); TCS=Total Combined Score (Rhinoconjunctivitis DSS + Rhinoconjunctivitis DMS); CI=Confidence Interval

Analyses were based on the full analysis set (FAS), which included all randomized and treated participants. Participants were analyzed according to the treatment group to which they were randomized.

*Non-parametric analysis for TCRS, Rhinitis DSS, and TCS endpoints; Parametric analysis using zero-inflated log-normal model for Rhinitis DMS endpoint.

†Number of participants in analyses.

‡For TCRS, Rhinitis DSS, and TCS endpoints, the estimated group medians are reported. Treatment difference and that relative to placebo is based on estimated group medians. For Rhinitis DMS, the estimated group means are reported. Treatment difference and that relative to placebo is based on estimated group means.

§Difference relative to placebo computed as: (ODACTRA – placebo)/placebo x 100.

¶The pre-specified criteria for demonstration of efficacy was defined as a TCRS difference relative to placebo less than or equal to -15 percent, and the upper bound of the 95 percent confidence interval (CI) of TCRS difference relative to placebo less than or equal to -10 percent.

Adults

Study 2 (European Field Efficacy Study)

This double-blind, placebo-controlled, randomized field efficacy study evaluated adult participants 18 through 66 years of age comparing ODACTRA (N=318) and placebo (N=338) administered as a sublingual tablet daily for a duration of approximately 12 months. Participants in this study had a history of symptomatic allergic rhinitis when exposed to house dust and were sensitized to D. farinae and/or D. pteronyssinus as determined by house dust mite specific IgE testing. At study entry, participants were required to be symptomatic despite taking symptom-relieving allergy medications during the baseline period.

In this study, 46% of participants had asthma, 97% had conjunctivitis and 67% were polysensitized to other allergens in addition to HDM, including trees, grass, weeds, animal danders and molds. The study population was 98% White, <1% African American, and <1% Asian; 50% of participants were female. The mean age of participants in this study was 32 years. The primary efficacy endpoint was the difference relative to placebo in the average TCRS during the last 8 weeks of treatment. The mean Rhinitis DSS at baseline was 7.95 out of 12 for the treatment arm and 8.00 out of 12 total points for the placebo arm. The results of this study are shown in Table 7.

Table 7: Total Combined Rhinitis Score (TCRS), Rhinitis Daily Symptom Score (DSS), Rhinitis Daily Medication Score (DMS), and Total Combined Score (TCS) During the Last 8 Weeks of Treatment with ODACTRA in Participants 18 Years of Age and Older (Study 2, European Field Efficacy Study)
Endpoint* | ODACTRA (n)† Score‡ | Placebo (n)† Score‡ | Treatment Difference (ODACTRA - Placebo) | Difference Relative to Placebo§ Estimate (95% CI)
Primary Endpoint
TCRS¶ | (318) 5.71 | (338) 6.81 | -1.09 | -16.1% (-25.8%, -5.7%)
Secondary Endpoints
Rhinitis DSS¶ | (318) 2.84 | (338) 3.31 | -0.47 | -14.1% (-23.8%, -3.9%)
Rhinitis DMS¶ | (318) 2.32 | (338) 2.86 | -0.54 | -18.9% (-34.7%, -1.3%)
TCS# | (241) 7.91 | (257) 9.12 | -1.21 | -13.2% (-23.7%, -1.5%)

TCRS=Total Combined Rhinitis Score (Rhinitis DSS + Rhinitis DMS); TCS=Total Combined Score (Rhinoconjunctivitis DSS + Rhinoconjunctivitis DMS); CI=Confidence Interval

*Parametric analysis using analysis of covariance model for all endpoints.

†Number of participants in analyses.

‡The estimated group least squares means are reported. Treatment difference and that relative to placebo is based on estimated group least squares means.

§Difference relative to placebo computed as: (ODACTRA – placebo)/placebo x 100.

¶Analysis based on FAS-MI: full analysis set with multiple imputations. The analysis treats participants who discontinued the study before the efficacy assessment period as placebo participants. For the primary analysis (FAS-MI) only the absolute difference was pre-specified. Additional analyses describing the corresponding pre-specified relative differences to placebo for the full analysis set (FAS): TCRS: -18.1% (-27.6%, -7.7%); rhinitis DSS: -16.2% (-25.7%, -5.8%); and rhinitis DMS: -21.4% (-36.6%, -3.2%).

#Participants from Serbia and Croatia were excluded from the analysis of TCS because the preferred formulations of antihistamine eyedrops were not available in these countries at the time the study was conducted. The TCS analysis is based on the full analysis set (FAS). All available data used to its full extent, i.e. participants who provided data during the efficacy assessment period.

Study 3 (Environmental Exposure Chamber Study)

This double-blind, placebo-controlled, randomized EEC study evaluated adult participants 18 through 58 years of age comparing ODACTRA (N=42) and placebo (N=41) administered as a sublingual tablet daily for approximately 24 weeks. Participants had a history of symptomatic allergic rhinitis and were sensitized to D. farinae and/or D. pteronyssinus as determined by HDM specific IgE. In this study, 23% of participants had asthma, 87% had conjunctivitis, and 84% were polysensitized to other allergens in addition to HDM, including tree, grass, weed, animal danders and molds. The participant population was 90% White, <1% African American, 8% Asian, and 43% female. The mean age of participants was 27 years.

The primary endpoint was the difference relative to placebo in the average TNSS at Week 24. The Total Nasal Symptom Score (TNSS) represents the sum of 4 nasal symptoms (runny nose, stuffy nose, sneezing, and itchy nose). Secondary endpoints were the differences relative to placebo in the average TNSS at Weeks 8 and 16 and average Total Symptom Score (TSS) at Week 24, which represents the sum of TNSS plus 2 ocular symptoms (gritty/itchy eyes and watery eyes). Baseline TNSS following house dust mite EEC challenge prior to treatment was 7.74 out of 12 total points for ODACTRA and 7.32 out of 12 total points for placebo. The results of this study are shown in Table 8.

Table 8: Total Nasal Symptom Score (TNSS) and Total Symptom Score (TSS) During HDM-Allergen Challenge (Study 3, Environmental Exposure Chamber Study)
Endpoint* | ODACTRA (n)† Score‡ | Placebo (n)† Score‡ | Treatment Difference (ODACTRA - Placebo) | Difference Relative to Placebo§ Estimate (95% CI)
Primary Endpoint
TNSS – Week 24 | (36) 3.83 | (34) 7.45 | -3.62 | -48.6% (-60.2%, -35.3%)
Secondary Endpoints
TNSS – Week 8 | (40) 5.34 | (39) 6.71 | -1.37 | -20.4% (-33.3%, -6.8%)
TNSS – Week 16 | (39) 4.82 | (38) 6.90 | -2.08 | -30.1% (-42.3%, -16.8%)
TSS – Week 24 | (36) 4.43 | (34) 9.27 | -4.84 | -52.2% (-65.0%, -37.0%)

TNSS=Total Nasal Symptom Score; TSS=Total Symptom Score (TNSS + total ocular symptom score); CI=Confidence Interval

*Parametric analysis using analysis of covariance for all endpoints.

†Number of participants in analyses.

‡The estimated group least squares means are reported. Treatment difference and that relative to placebo is based on estimated group least squares means.

§Difference relative to placebo computed as: (ODACTRA – placebo)/placebo x 100.

Children

Study 6 (European and North American Field Efficacy Study)

Study 6 was a double-blind, placebo-controlled, randomized field efficacy study conducted in Europe, the United States and Canada for a duration of approximately 12 months, that compared the efficacy of ODACTRA (N=693) to placebo (N=706) in the treatment of HDM allergic rhinitis/rhinoconjunctivitis with or without asthma in children 5 through 11 years of age.

Participants were enrolled if they, during the previous year prior to screening, had a history of HDM allergic rhinitis/ rhinoconjunctivitis with symptoms despite having received symptom-relieving medication and were sensitized to D. farinae and/or D. pteronyssinus as determined by house dust mite specific IgE testing. At study entry, participants were required to be symptomatic despite taking symptom-relieving allergy medications at enrollment.

Of the participants treated with ODACTRA, mean age was 8 years, 67% were male, 99% White, <1% Black or African American, <1% multiple race, <1% Asian, and <1% American Indian or Alaska Native. Participant demographics in the placebo group were similar to the ODACTRA group. In the ODACTRA group, 37% of participants had asthma and 54% were sensitized to other allergens in addition to HDM; the treatment groups were similar with respect to these baseline characteristics.

Together with the parents/caregivers, participants recorded their symptoms and medication use daily in an eDiary for 21 days prior to randomization (baseline) to determine eligibility for the study. Symptoms and medication use were recorded daily during specified eDiary periods during the study. The primary efficacy assessment period was the last 8 weeks of the 1 year treatment period. Based on the data recorded in the eDiaries, the Total Combined Rhinitis Score (TCRS), daily symptom scores (DSS) and daily medication scores (DMS) for rhinitis were calculated. Daily symptoms included four nasal symptoms (runny nose, stuffy nose, sneezing, and itchy nose) and two ocular symptoms (gritty/itchy eyes and watery eyes). Each of these symptoms was individually graded by participants on a scale of 0 (none) to 3 (severe) and then summed. Participants in active and placebo arms of this study were provided with and allowed to take symptom-relieving allergy medications (including oral and ocular antihistamines and nasal corticosteroids) during the study as needed. The DMS measured the use of these standard symptom-relieving allergy medications. Predefined daily maximum scores were assigned to each class of rhinitis and conjunctivitis medication as 0=none, 6=oral antihistamine, 6=ocular antihistamine, and 8=nasal corticosteroid.

The primary endpoint was the difference between the treatment and placebo groups in the average TCRS during the last approximately 8 weeks of treatment. The TCRS represents the sum of the rhinitis DSS and the rhinitis DMS. Other secondary endpoints in this study included the rhinitis DSS, the rhinitis DMS, and Total Combined Score (TCS). The TCS is the sum of the rhinoconjunctivitis DSS and rhinoconjunctivitis DMS, assessed during the last 8 weeks of treatment.

The baseline mean TCRS was approximately 18 in both treatment groups (on a scale of 0-24) and the mean rhinitis DSS and rhinitis DMS were approximately 8 and 10, respectively, in both treatment groups (on a scale of 0-12).

The results of this study are shown in Table 9.

Table 9: Total Combined Rhinitis Score (TCRS), Rhinitis Daily Symptom Score (DSS), Rhinitis Daily Medication Score (DMS), and Total Combined Score (TCS) During the Last 8 Weeks of Treatment with ODACTRA in Participants 5 through 11 Years of Age (Study 6, European and North American Field Efficacy Study)
Endpoint* | ODACTRA (n)† Score‡ | Placebo (n)† Score‡ | Treatment Difference (ODACTRA - Placebo) | Difference Relative to Placebo§ Estimate (95% CI)
Primary Endpoint¶
TCRS | (693) 3.4 | (706) 4.4 | -1.0 | -22.0% (-31.1; -12.0)
Secondary Endpoints
Rhinitis DSS | (693) 1.5 | (706) 1.9 | -0.4 | -22.2% (-30.8; -12.8)
Rhinitis DMS | (693) 1.4 | (706) 1.9 | -0.5 | -25.3% (-38.3; -10.5)
TCS | (693) 4.0 | (706) 5.2 | -1.1 | -22.2% (-31.5; -12.0)

TCRS=Total Combined Rhinitis Score (Rhinitis DSS + Rhinitis DMS); TCS=Total Combined Score (Rhinoconjunctivitis DSS + Rhinoconjunctivitis DMS); CI=Confidence Interval.

*Primary analysis using mixed model analysis of covariance.

†n: number of participants with observations contributing to the analysis.

Analysis based on full analysis set, which included all randomized and treated participants. Participants were analyzed according to the treatment group to which they were randomized.

‡The estimated group least squares means are reported. Treatment difference and that relative to placebo is based on estimated group least squares means.

§Difference relative to placebo computed as: (ODACTRA – placebo)/placebo x 100, 95 CI.

¶The pre-specified criteria for demonstration of efficacy were defined as a TCRS difference relative to placebo less than or equal to -15 percent, and the upper bound of the 95 percent confidence interval of TCRS difference relative to placebo less than or equal to -10 percent.

16 HOW SUPPLIED/STORAGE AND HANDLING

ODACTRA 12 SQ-HDM tablets are white to off-white, circular freeze-dried sublingual tablets with a debossed pentagon detail on one side.

ODACTRA is supplied as follows:

3 blister packages of 10 tablets (30 tablets total). NDC 52709-1701-3

Store at controlled room temperature, 20ºC-25ºC (68ºF-77ºF). Store in the original package until use to protect from moisture.

17 PATIENT COUNSELING INFORMATION

Advise patients (or their parents/guardians) to read the FDA-approved patient labeling (Medication Guide) and to keep ODACTRA and all medicines out of the reach of children.

Severe Allergic Reactions

- Advise patients (or their parents/guardians) that ODACTRA may cause life-threatening systemic or local allergic reactions, including anaphylaxis. Educate patients (or their parents/guardians) about the signs and symptoms of these allergic reactions [see Warnings and Precautions (5.1)]. The signs and symptoms of a severe allergic reaction may include: syncope, dizziness, hypotension, tachycardia, dyspnea, wheezing, bronchospasm, chest discomfort, cough, abdominal pain, vomiting, diarrhea, rash, pruritus, flushing, and urticaria.
- Ensure that patients (or their parents/guardians) have epinephrine and instruct patients (or their parents/guardians) in its proper use. Instruct patients (or their parents/guardians) who experience a severe allergic reaction to seek immediate medical care, discontinue ODACTRA, and resume treatment only when advised by a healthcare professional to do so [see Warnings and Precautions (5.1).]
- Advise patients to read the patient information for epinephrine.
- Inform patients (or their parents/guardians) that the first dose of ODACTRA must be administered in a healthcare setting under the supervision of a healthcare professional and that they will be monitored for at least 30 minutes to watch for signs and symptoms of life-threatening systemic or local allergic reaction [see Warnings and Precautions (5.1)].
- Because of the risk of upper airway compromise, instruct patients (or their parents/guardians) with persistent and escalating adverse reactions in the mouth or throat to discontinue ODACTRA and to contact their healthcare professional [see Warnings and Precautions (5.2)].
- Because of the risk of eosinophilic esophagitis, instruct patients (or their parents/guardians) with severe or persistent symptoms of esophagitis to discontinue ODACTRA and to contact their healthcare professional [see Warnings and Precautions (5.3)].

Asthma

- Instruct patients (or their parents/guardians) with asthma that if they have difficulty breathing or if their asthma becomes difficult to control, they should stop taking ODACTRA and contact their healthcare professional immediately [see Warnings and Precautions (5.4)].

Administration Instructions

- Instruct patients (or their parents/guardians) to carefully remove the foil from the blister unit with dry hands and then take the sublingual tablet immediately by placing it under the tongue where it will dissolve within 10 seconds. Instruct patients to avoid swallowing for at least 1 minute. Also instruct patients to wash their hands after handling the tablet, and to avoid food or beverages for 5 minutes after taking the tablet [see Dosage and Administration (2.2)].
- Advise patients (or their parents/guardians) who miss more than one dose of ODACTRA to contact their healthcare professional before restarting [see Warning and Precautions (5.1)].

Manufactured for: ALK-Abelló A/S

ALK-Abelló A/S, Bøge Allé 6-8, DK-2970 Hørsholm, Denmark

U.S. License No. 1292

Manufactured by:
Catalent Pharma Solutions Limited, Blagrove,
Swindon, Wiltshire, SN5 8RU UK

© 2025 ALK-Abelló A/S
All rights reserved.

MEDICATION GUIDE
ODACTRA™ (OH-dack-trah)
House Dust Mite (Dermatophagoides farinae and Dermatophagoides pteronyssinus) Allergen Extract
Sublingual Tablets

Carefully read this Medication Guide before you or your child starts taking ODACTRA and each time you get a refill. This Medication Guide does not take the place of talking with your healthcare provider about your or your child’s medical condition or treatment. Talk with your healthcare provider if there is something you do not understand or if you want to learn more about ODACTRA.

What is the Most Important Information I Should Know about ODACTRA?
ODACTRA can cause severe allergic reactions that may be life-threatening. Stop taking ODACTRA and get medical treatment right away if you or your child has any of the following symptoms after taking ODACTRA:

- Trouble breathing
- Throat tightness or swelling
- Trouble swallowing or speaking
- Dizziness or fainting
- Rapid or weak heartbeat
- Severe stomach cramps or pain, vomiting, or diarrhea
- Severe flushing or itching of the skin

For home administration of ODACTRA, your doctor will prescribe epinephrine, a medicine you can use if you or your child has a severe allergic reaction after taking ODACTRA. Your doctor will train and instruct you on the proper use of epinephrine.
Talk to your doctor or read the epinephrine patient information if you have any questions about the use of epinephrine.

What is ODACTRA?
ODACTRA is a prescription medicine used for sublingual (under the tongue) immunotherapy to treat house dust mite allergies that can cause sneezing, runny or itchy nose, stuffy or congested nose, or itchy and watery eyes. ODACTRA may be prescribed for persons 5 through 65 years of age who are allergic to house dust mites.
ODACTRA is NOT a medication that gives immediate relief for symptoms of house dust mite allergy.

Who Should Not Take ODACTRA?
You or your child should not take ODACTRA if you or your child:

- has severe, unstable or uncontrolled asthma
- had a severe allergic reaction in the past that included any of these symptoms:
  - Trouble breathing
  - Dizziness or fainting
  - Rapid or weak heartbeat
- has ever had difficulty with breathing due to swelling of the throat or upper airway after using any sublingual immunotherapy before.
- has ever been diagnosed with eosinophilic esophagitis.
- is allergic to any of the inactive ingredients contained in ODACTRA. The inactive ingredients contained in ODACTRA are: gelatin, mannitol, and sodium hydroxide.

What Should I Tell My Doctor Before Taking ODACTRA?
Your doctor may decide that ODACTRA is not the best treatment if you or your child:

- has asthma, depending on how severe it is.
- suffers from lung disease such as chronic obstructive pulmonary disease (COPD).
- suffers from heart disease such as coronary artery disease, an irregular heart rhythm, or you or your child has hypertension that is not well controlled.
- is pregnant, plans to become pregnant during the time you will be taking ODACTRA, or is breast-feeding.
- is unable or unwilling to administer epinephrine to treat a severe allergic reaction to ODACTRA.
- is taking certain medicines that enhance the likelihood of a severe reaction, or interfere with the treatment of a severe reaction. These medicines include:
  - beta blockers and alpha-blockers (prescribed for high blood pressure)
  - cardiac glycosides (prescribed for heart failure or problems with heart rhythm)
  - diuretics (prescribed for heart conditions and high blood pressure)
  - ergot alkaloids (prescribed for migraine headache)
  - monoamine oxidase inhibitors or tricyclic antidepressants (prescribed for depression)
  - thyroid hormone (prescribed for low thyroid activity).
- is receiving allergy shots or other immunotherapy under the tongue. Use of more than one of these types of medicines together may increase the likelihood of a severe allergic reaction.

You should tell your doctor if you or your child is taking or has recently taken any other medicines, including medicines obtained without a prescription and herbal supplements. Keep a list of them and show it to your doctor and pharmacist each time you get a new supply of ODACTRA. Ask your doctor or pharmacist for advice before taking ODACTRA.
ODACTRA is not indicated for use in children under 5 years of age or adults over 65 years of age.

Are there any Reasons to Stop Taking ODACTRA?
Stop ODACTRA and contact your doctor if you or your child has any of the following after taking ODACTRA:

- Any type of a serious allergic reaction
- Throat tightness that worsens or swelling of the tongue or throat that causes trouble speaking, breathing, or swallowing
- Asthma or any other breathing condition that gets worse
- Dizziness or fainting
- Rapid or weak heartbeat
- Severe stomach cramps or pain, vomiting, or diarrhea
- Severe flushing or itching of the skin
- Heartburn, difficulty swallowing, pain with swallowing, or chest pain that does not go away or worsens

Also, stop taking ODACTRA following mouth surgery procedures (such as tooth removal), tooth loss or if you or your child develops any mouth infections, ulcers or cuts in the mouth or throat to allow complete healing.

How Should I Take ODACTRA?
Take ODACTRA exactly as your doctor tells you.
ODACTRA is a prescription medicine that is placed under the tongue.

- Take the tablet from the blister package after carefully removing the foil with dry hands.
- Place the tablet immediately under the tongue where it will dissolve within 10 seconds. Do not swallow for at least 1 minute.
- Do not take ODACTRA with food or beverage. Food and beverage should not be taken for the following 5 minutes.
- Wash hands after taking the tablet.

Take the first tablet of ODACTRA in the prescribing doctor’s office. After taking the first tablet, you or your child will be watched for at least 30 minutes for symptoms of a serious allergic reaction.
If you tolerate the first tablet of ODACTRA, you or your child will continue ODACTRA therapy at home by taking one tablet every day. Children should be given each tablet of ODACTRA by an adult who will watch for any symptoms of a serious allergic reaction.
Take ODACTRA every day for as long as your doctor prescribes it, even if you have no allergy symptoms.
If you or your child forgets to take ODACTRA, do not take two tablets. Take the next tablet at your normal scheduled time the next day. If you or your child misses more than one dose of ODACTRA, contact your healthcare provider before restarting.
You or your child may begin to have relief of your house dust mite allergy symptoms within 2 to 3 months of starting ODACTRA.

What are the Possible Side Effects of ODACTRA?
The most commonly reported side effects were throat irritation/tickle, itching in the mouth or ears, swelling of the back of the mouth, lips or tongue, tongue pain, nausea, throat swelling, stomach pain, tongue ulcer/sore on the tongue, and mouth ulcer/sore in the mouth, diarrhea, vomiting, and food tastes different. These side effects, by themselves, were not dangerous or life-threatening. Typically, these common side effects begin within the first week of starting ODACTRA and may reoccur for up to two weeks. These common side effects experienced after taking the first tablet typically last up to one hour.
ODACTRA can cause severe allergic reactions that may be life-threatening. Symptoms of allergic reactions to ODACTRA include:

- Trouble breathing
- Throat tightness or swelling
- Trouble swallowing or speaking
- Dizziness or fainting
- Rapid or weak heartbeat
- Severe stomach cramps or pain, vomiting, or diarrhea
- Severe flushing or itching of the skin

For additional information on the possible side effects of ODACTRA talk with your doctor or pharmacist. You may report side effects to the U.S. Food and Drug Administration (FDA) at 1-800-FDA-1088 or www.fda.gov/medwatch.

How Should I Store ODACTRA?
Keep ODACTRA out of the reach of children.
Throw away any unused ODACTRA after the expiration date which is stated on the carton and blister pack after “EXP.”
Store ODACTRA in a dry place at room temperature, 20ºC to 25ºC (68ºF to 77ºF), in the original package.

General Information about ODACTRA
Medicines are sometimes prescribed for purposes other than those listed in a Medication Guide. Do not use ODACTRA for a condition for which it was not prescribed. Do not give ODACTRA to other people, even if they have the same symptoms. It may harm them.
This Medication Guide summarizes the most important information about ODACTRA. If you would like more information, talk with your doctor. You can ask your doctor or pharmacist for information about ODACTRA that was written for healthcare professionals.
For more information, go to: www.ODACTRA.com or call 1-855-782-9323 (toll-free).

Manufactured for: ALK-Abelló A/S
ALK-Abelló A/S, Bøge Allé 6-8, DK-2970 Hørsholm, Denmark
U.S. License No. 1292
Manufactured by:
Catalent Pharma Solutions Limited, Blagrove,
Swindon, Wiltshire, SN5 8RU UK
© 2025 ALK-Abelló A/S
All rights reserved.

This Medication Guide has been approved by the U.S. Food and Drug Administration. Revised: 2/2025

PRINCIPAL DISPLAY PANEL

NDC 52709-1701-3
House Dust Mite (Dermatophagoides farinae and Dermatophagoides pteronyssinus) Allergen Extract
ODACTRA
Sublingual Tablets
3 blister packages of 10 tablets (30 tablets total).